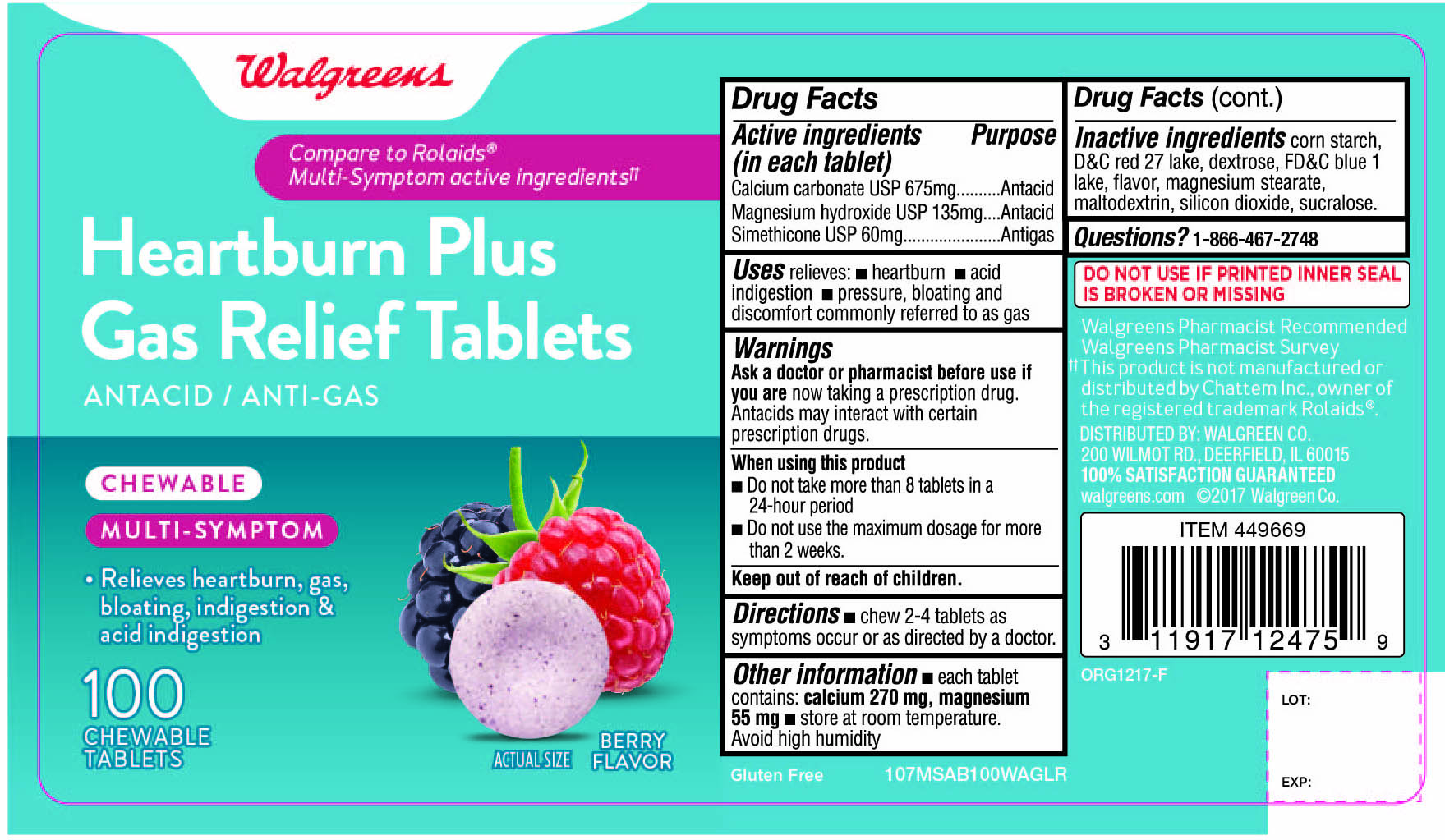 DRUG LABEL: Heartburn Plus Gas Relief Chewable Multi Symptom
NDC: 0363-0107 | Form: TABLET, CHEWABLE
Manufacturer: WALGREEN CO.
Category: otc | Type: HUMAN OTC DRUG LABEL
Date: 20180101

ACTIVE INGREDIENTS: CALCIUM CARBONATE 675 mg/1 1; MAGNESIUM HYDROXIDE 135 mg/1 1; DIMETHICONE 60 mg/1 1
INACTIVE INGREDIENTS: STARCH, CORN; D&C RED NO. 27; DEXTROSE; FD&C BLUE NO. 1; MAGNESIUM STEARATE; MALTODEXTRIN; SILICON DIOXIDE; SUCRALOSE

Walgreens Heartburn Plus Gas Relief ANTACID ANTIGAS 100 CHEWABLE Tablets Berry Flavor

Drug Facts

Active ingredients

(in each tablet)
Calcium carbonate USP 675 mg
Magnesium hydroxide USP 135 mg

Simethicone USP 60mg

Purpose

Antacid

Antacid

Antigas

Uses

relieves:

- heartburn
- acid indigestion
- pressure, bloating and discomfort commonly referred to as gas

Warnings

Ask a doctor or pharmacist before use if you are

now taking a prescription drug.

Antacids may interact with certain prescription drugs.

When using this product

- Do not take more than 8 tablets in a 24-hour period,
- Do not use the maximum dosage for more than 2 weeks

Directions

- chew 2 to 4 tablets as symptoms occur or as directed by a doctor.

Other information

- each tablet contains: calcium 270 mg, magnesium 55 mg
- store at room temperature
- Avoid high humidity.

Inactive ingredients

corn starch, D & C red 27 lake, dextrose, FD & C blue 1 lake, , flavor, magnesium stearate, maltodextrin, silicon dioxide, sucralose.

Questions?

1-866-467-2748

PRINCIPAL DISPLAY PANEL

Walgreens

Compare to Rolaids® Multi-Symptom active ingredients††

Heartburn Plus Gas Relief Tablets

Antacid/ AntiGas

CHEWABLE

MULTI-SYMPTOM

- Relieves heartburn, gas ,bloating indigestion & acid indigestion

Berry FLAVOR

100 CHEWABLE TABLETS

††This product is not manufactured or distributed by Chattem Inc., owner of the registered trademark ROLAIDS®

Walgreens Pharmacist Survey

Walgreens Pharmacist Recommended

DISTRIBUTED BY: WALGREEN CO.

200 WILMOT RD.,DEERFIELD,IL 60015

Walgreens 100% SATISFACTION GUARANTEED

Walgreens.com ©2017 Walgreen Co.